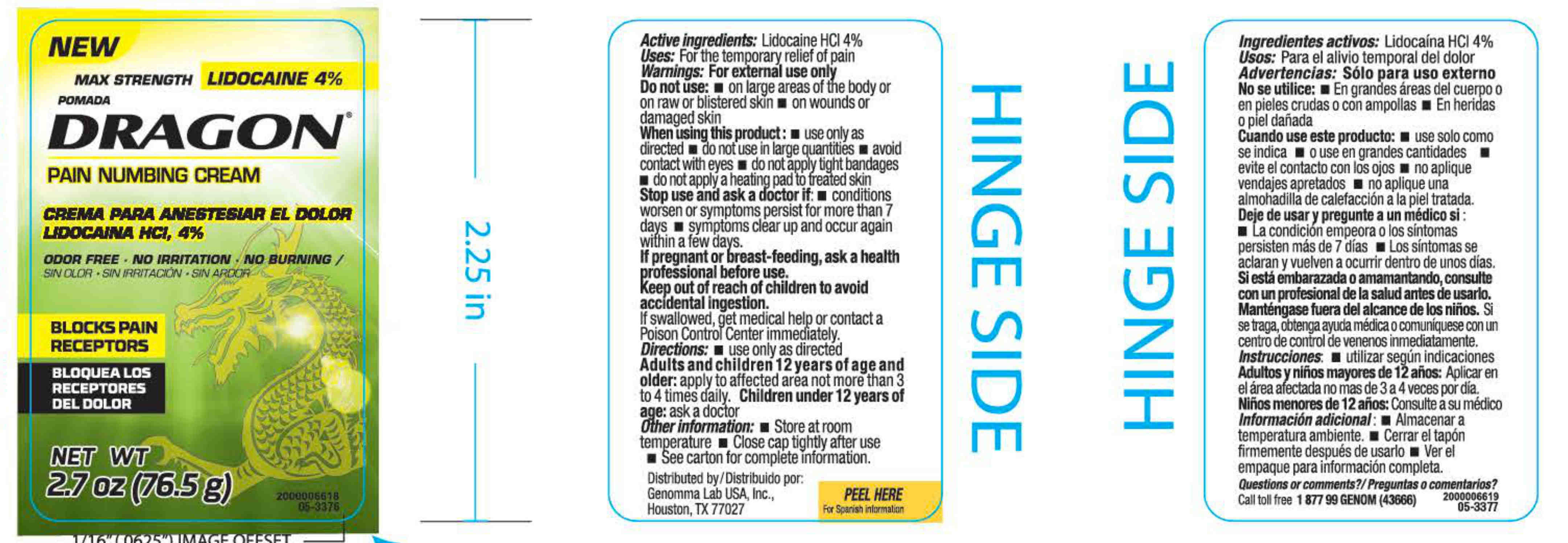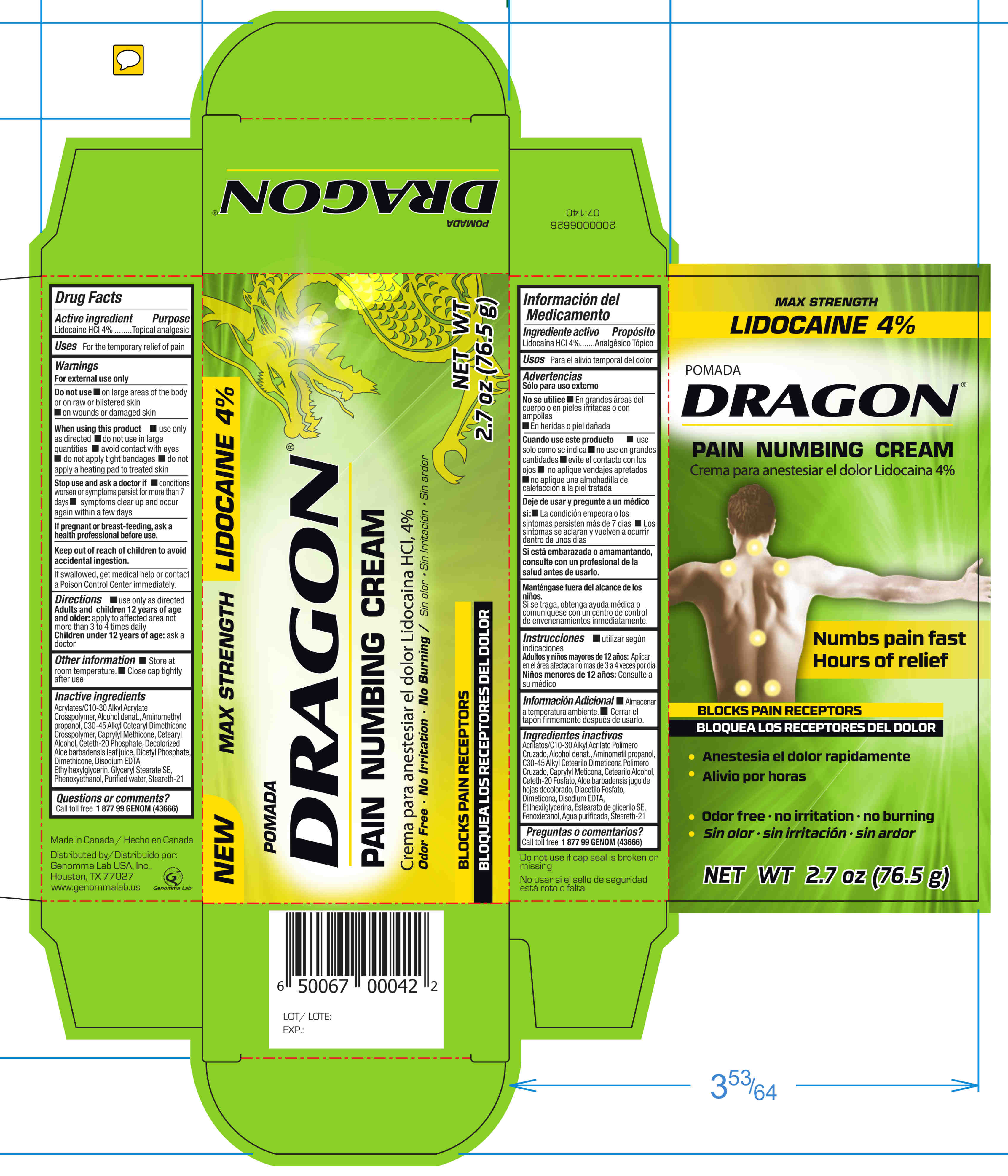 DRUG LABEL: POMODA DRAGON PAIN NUMBING
NDC: 65365-284 | Form: CREAM
Manufacturer: SIGAN INDUSTRIES GROUP
Category: otc | Type: HUMAN OTC DRUG LABEL
Date: 20170731

ACTIVE INGREDIENTS: LIDOCAINE HYDROCHLORIDE 40 mg/1 g
INACTIVE INGREDIENTS: GLYCERYL STEARATE SE; CETETH-20 PHOSPHATE; ETHYLHEXYLGLYCERIN; PHENOXYETHANOL; WATER; STEARETH-21

MAX STRENGTH POMADA DRAGON PAIN NUMBING CREAM

ACTIVE INGREDIENT

LIDOCAINE HCI 4%

PURPOSE

TOPICAL ANALGESIC

USES

FOR TEMPORARY RELIEF OF PAIN

WARNINGS

FOR EXTERNAL USE ONLY

DO NOT USE

ON LARGE AREAS OF THE BODY OR ON RAW OR BLISTERED SKIN

ON WOUNDS OR DAMAGED SKIN

WHEN USING THIS PRODUCT

USE ONLY AS DIRECTED.

DO NOT USE IN LARGE QUANTITIES

AVOID CONTACT WITH EYES

DO NOT APPLY TIGHT BANDAGES

DO NOT APPLY A HEATING PAD TO TREATED SKIN

STOP USE AND ASK A DOCTOR IF

CONDITIONS WORSEN OR SYMPTOMS PERSIST FOR MORE THAN 7 DAYS.

SYMPTOMS CLEAR UP AND OCCUR AGAIN WITHIN A FEW DAYS

IF PREGNANT OR BREAST-FEEDING

ASK A HEALTH PROFESSIONAL BEFORE USE

KEEP OUT OF REACH OF CHILDREN TO AVOID ACCIDENTAL INGESTION

IF SWALLOWED, GET MEDICAL HELP OR CONTACT A POISON CONTROL CENTER IMMEDIATELY

DIRECTIONS

USE ONLY AS DIRECTED

ADULTS AND CHILDREN 12 YEARS OF AGE AND OLDER: APPLY TO AFFECTED AREA NOT MORE THAN 3 TO 4 TIMES DAILY

CHILDREN UNDER 12 YEARS OF AGE: ASK A DOCTOR

OTHER INFORMATION

STORE AT ROOM TEMPERATURE

CLOSE CAP TIGHTLY AFTER USE

QUESTION SOR COMMENTS?

CALL TOLL FREE 1 877 99 GENOM (43666)

INACTIVE INGREDIENTS

ACRYLATES/C10-30 ALKYL CRYLATE CROSSPOLYMER, ALCOHOL DENAT., AMINOMETHYL PROPANOL, C30-45 ALKYL CETEARLYL DIMETHICONE CROSSPOLYMER, CAPRYLYL METHICONE, CETEARYL ALCOHOL, CETETH-20 PHOSPHATE, DECOLORIZED ALOE BARBADENSIS LEAF JUICE, DICETYL PHOSPHATE DIMETHICONE, DISODIUM EDTA, ETHYLHEXYGLYCERIN, GLYCERYL STARATE SE, PHENOXYETHANOL, PURIFIED WATER, STEARETH-21

PACKAGE LABEL DISPLAY PANEL

NEW MAX STRENGTH LIDOCAINE 4%

POMADA DRAGON PAIN NUMBING CREAM

CREMA PARA ANESTESIAR EL DOLOR LIDOCAINA HCI 4%

ORDOR FREE. NO IRRITATION, NO BURNING./ SIN OLOR. SIN IRRITACIÓN. SIN ARDOR

BLOCKS PAIN RECEPTORS/ BLOQUEA LOS RECEPTORES DEL DOLOR

NET WT 2.7 OZ (76.5g)